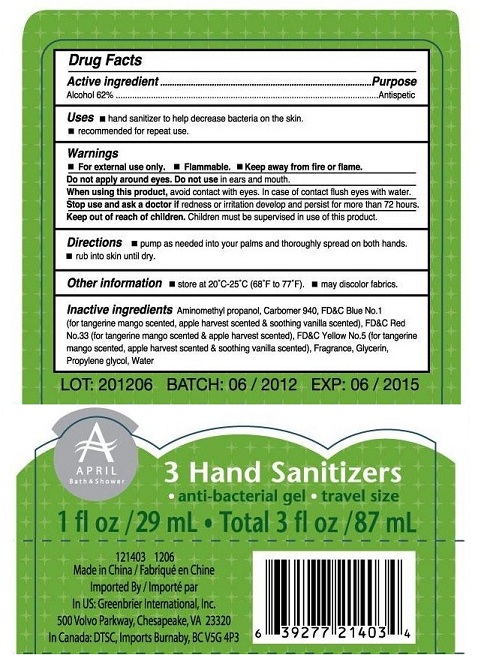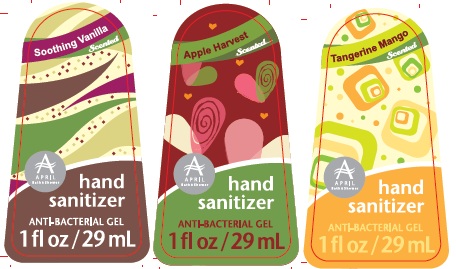 DRUG LABEL: 3 Hand Sanitizers
NDC: 33992-1400 | Form: KIT | Route: TOPICAL
Manufacturer: Greenbrier International, Inc.
Category: otc | Type: HUMAN OTC DRUG LABEL
Date: 20120618

ACTIVE INGREDIENTS: ALCOHOL 62 mL/100 mL; ALCOHOL 62 mL/100 mL; ALCOHOL 62 mL/100 mL
INACTIVE INGREDIENTS: AMINOMETHYLPROPANOL; CARBOMER HOMOPOLYMER TYPE B/C (ALLYL PENTAERYTHRITOL CROSSLINKED); FD&C BLUE NO. 1; D&C RED NO. 33; FD&C YELLOW NO. 5; GLYCERIN; PROPYLENE GLYCOL; WATER; AMINOMETHYLPROPANOL; CARBOMER HOMOPOLYMER TYPE B/C (ALLYL PENTAERYTHRITOL CROSSLINKED); FD&C BLUE NO. 1; D&C RED NO. 33; FD&C YELLOW NO. 5; GLYCERIN; PROPYLENE GLYCOL; WATER; AMINOMETHYLPROPANOL; CARBOMER HOMOPOLYMER TYPE B/C (ALLYL PENTAERYTHRITOL CROSSLINKED); FD&C BLUE NO. 1; D&C RED NO. 33; FD&C YELLOW NO. 5; GLYCERIN; PROPYLENE GLYCOL; WATER

3 Hand Sanitizers - Antibacterial gel - travel size

Active Ingredient

Alcohol 62%

Purpose

Antiseptic

Uses

- Hand sanitizer to help decrease bacteria on the skin
- recommended for repeat use

Warnings

- For external use only
- Flammable
- Keep away from fire or flame.

Do not apply around eyes. Do not use in ears and mouth.

When using this product

avoid contact with eyes. In case of contact flush eyes with water.

Stop use and ask a doctor

if redness or irritation develop and persist for more than 72 hours

Keep out or reach of children.

Children must be supervised in use of this product.

Directions

- Pump as needed into your palms and thoroughly spread on both hands.
- rub into skin until dry.

Other information

store at 20C-25C (68F to 77F)

May discolor fabrics

Inactive Ingredients

Aminomethyl propanol, Carbomer 940, FDandC Blue No. 1 (for tangerine mango scented, apple harvest scented and soothing vanilla scented), FDandC Red No. 33 (for tangerine mango scented and apple harvest scented), FDandC Yellow No. 5 (for tangerine mango scented, apple harvest scented and soothing vanilla scented), Fragrance, Glycerin, Propylene glycol, Water.

DESCRIPTION

3 Hand Sanitizers

Antibacterial gel - travel size

1fl oz/29ml - Total 3fl oz / 87mL

121403 1206

Made in China
Imported by
In US: Greenbrier International, Inc. 500 Volvo Parkway, Chesapeake VA 23320
In Canada: DTSC, Imports Burnaby, BC VSG 4P3